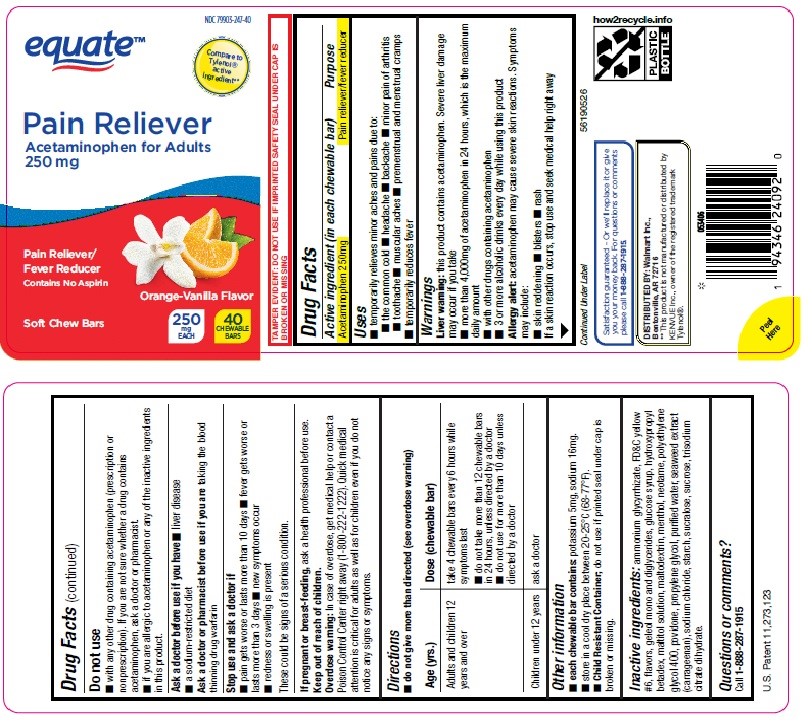 DRUG LABEL: Equate Pain Reliever Acetaminophen for Adults 250 mg
NDC: 79903-247 | Form: BAR, CHEWABLE
Manufacturer: Walmart Inc
Category: otc | Type: HUMAN OTC DRUG LABEL
Date: 20240321

ACTIVE INGREDIENTS: ACETAMINOPHEN 250 mg/1 1
INACTIVE INGREDIENTS: POLYETHYLENE GLYCOL 400; PROPYLENE GLYCOL; POVIDONE K30; CORN SYRUP; HYDROXYPROPYL BETADEX; NEOTAME; AMMONIUM GLYCYRRHIZATE; GLYCERYL MONO AND DIPALMITOSTEARATE; SUCRALOSE; SODIUM CHLORIDE; CARRAGEENAN; TRISODIUM CITRATE DIHYDRATE; SUCROSE; MALTITOL; MALTODEXTRIN; LEVOMENTHOL; FD&C YELLOW NO. 6; WATER; STARCH, CORN

Equate Pain Reliever Acetaminophen for Adults 250 mg

Active ingredient (in each chewable bar)

Acetaminophen 250mg

Purpose

Pain reliever/fever reducer

Uses

- temporarily relieves minor aches and pains due to:
- the common cold
- headache
- backache
- minor pain of arthritis
- toothache
- muscular aches
- premenstrual and menstrual cramps
- temporarily reduces fever

Warnings

Liver warning:this product contains acetaminophen. Severe liver damage may occur if you take

- more than 4,000mg of acetaminophen in 24 hours, which is the maximum daily amount
- with other drugs containing acetaminophen
- 3 or more alcoholic drinks every day while using this product.

Allergy alert:

acetaminophen may cause severe skin reactions. Symptoms may include:

- skin reddening
- blisters
- rash

If a skin reaction occurs, stop use and seek medical help right away

Do not Use

- with any other drug containing acetaminophen (prescription or nonprescription). If you are not sure whether a drug contains acetaminophen, ask a doctor or pharmacist.
- if you are allergic to acetaminophen or any of the inactive ingredients in this product.

Ask a doctor before use if you have

- liver disease
- a sodium-restricted diet

Ask a doctor or pharmacist before use if you aretaking the blood thinning drug warfarin

Stop use and ask a doctor if

- pain gets worse or lasts more than 10 days
- fever gets worse or lasts more than 3 days
- new symptoms occur
- redness or swelling is present

These could be signs of a serious condition.

PREGNANCY OR BREAST FEEDING

If pregnant or breast-feeding,ask a health professional before use.

Keep out of reach of children.

Overdose warning:

In case of overdose, get medical help or contact a Poison Control Center right away (1-800-222-1222). Quick medical attention is critical for adults as well as for children even if you do not notice any signs or symptoms.

Directions

- do not give more than directed (see overdose warning)

Age (yrs.) | Dose (chewable bar)
Adults and children 12 years and over | - take 4 chewable bars every 6 hours while symptoms last - do not take more than 12 chewable bars in 24 hours, unless directed by a doctor - do not use for more than 10 days unless directed by a doctor
Children under 12 years | ask a doctor

Other information

- each chewable bar contains: potassium 5mg, sodium 16mg.
- Store in a cool dry place between 20-25°C (68-77°F).
- Child Resistant Container;do not use if printed seal under cap is broken or missing.

Inactive ingredients:

ammonium glycyrrhizate, FD & C yellow #6, flavors, geleol mono and diglycerides, glucose syrup, hydroxypropyl betadex, maltitol solution, maltodextrin, menthol, neotame, polyethylene glycol 400, povidone, propylene glycol, purified water, seaweed extract (carrageenan), sodium chloride, starch, sucralose, sucrose, trisodium citrate dihydrate.

Questions or comments?

Call 1-888-287-1915

U.S. Patent 11,273,123

Principal Display Panel - Equate Pain Reliever Acetaminophen for Adults 250 mg-Orange Vanilla Flavor

NDC 79903-247-40

equate™

Compare to Tylenol®active ingredient**

Pain Reliever Acetaminophen for Adults 250 mg

Pain Reliever/Fever Reducer

Contains No Aspirin

Soft Chew Bars

Orange Vanilla Flavor

250 mg EACH 40 CHEWABLE BARS

TAMPER EVIDENT: DO NOT USE IF IMPRINTED SAFETY SEAL UNDER CAP IS BROKEN OR MISSING.